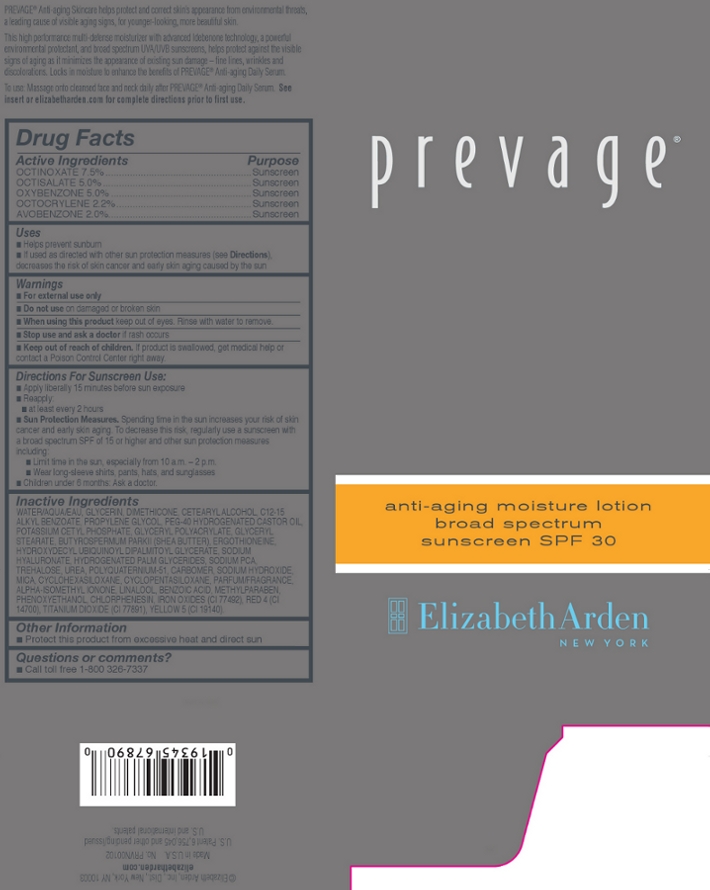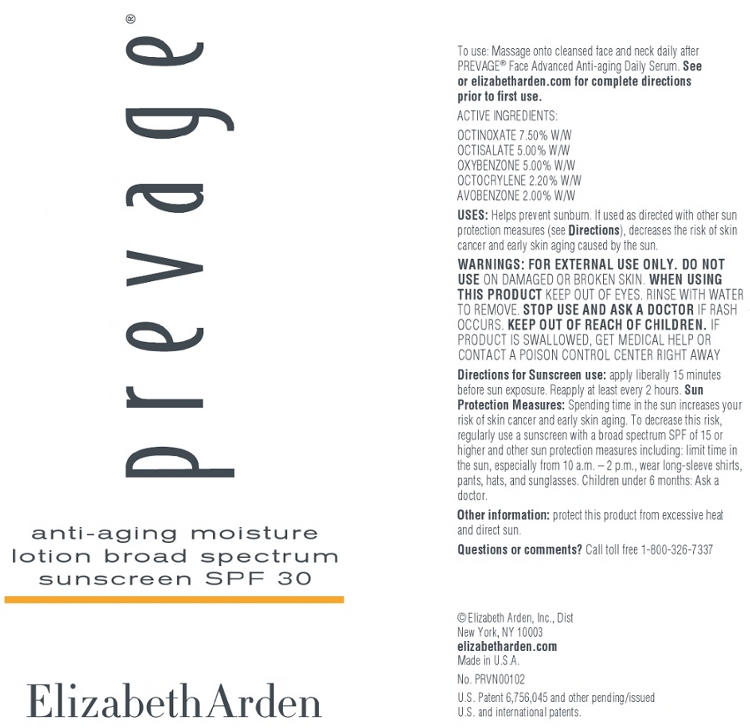 DRUG LABEL: Prevage Anti Aging Moisture Broad Spectrum Sunscreen SPF 30
NDC: 67938-0904 | Form: LOTION
Manufacturer: Elizabeth Arden, Inc
Category: otc | Type: HUMAN OTC DRUG LABEL
Date: 20130424

ACTIVE INGREDIENTS: OCTINOXATE 35 mg/50 mL; OCTISALATE 25 mg/50 mL; OXYBENZONE 25 mg/50 mL; OCTOCRYLENE 11 mg/50 mL; AVOBENZONE 10 mg/50 mL
INACTIVE INGREDIENTS: WATER; GLYCERIN; DIMETHICONE; CETOSTEARYL ALCOHOL; ALKYL (C12-15) BENZOATE; PROPYLENE GLYCOL; POLYOXYL 40 HYDROGENATED CASTOR OIL; POTASSIUM CETYL PHOSPHATE; GLYCERYL MONOSTEARATE; CYCLOMETHICONE 6; PHENOXYETHANOL; METHYLPARABEN; CYCLOMETHICONE 5; MICA; SODIUM PYRROLIDONE CARBOXYLATE; UREA; CHLORPHENESIN; BENZOIC ACID; SODIUM HYDROXIDE; TREHALOSE; HYALURONATE SODIUM

BB0904

DESCRIPTION

PREVAGE Anti-aging Skincare helps protect and correct skin’s appearance from environmental threats, a leading cause of visible aging signs, for younger-looking, more beautiful skin. This high performance multi-defense moisturizer with advanced Idebenone technology, a powerful environmental protectant, and broad spectrum UVA/UVB sunscreens, helps protect against the visible signs of aging as it minimizes the appearance of existing sun damage – fine lines, wrinkles and discolorations. Locks in moisture to enhance the benefits of PREVAGE Anti-aging Daily Serum.

INDICATIONS AND USAGE

To Use: Massage onto cleansed face and neck daily after PREVAGE Anti-aging Daily Serum.

Directions For Sunscreen Use: Apply liberally 15 minutes before sun exposure. Reapply: at least every 2 hours Sun Protection Measures. Spending time in the sun increases your risk of skin cancer and early skin aging. To decrease this risk, regularly use a sunscreen with a broad spectrum SPF of 15 or higher and other sun protection measures including: Limit time in the sun, especially from 10 a.m. – 2 p.m. Wear long-sleeve shirts, pants, hats, and sunglasses. Children under 6 months: Ask a doctor.

WARNINGS

For external use only.

Do not use on damaged or broken skin.

When using this product keep out of eyes. Rinse with water to remove.

Stop use and ask a doctor if rash occurs.

OTC - ACTIVE INGREDIENT

Active Ingredients: Octinoxate, 7.50% , Octisalate, 5.00%, Oxybenzone, 5.00%, Octocrylene, 2.20%, Avobenzone, 2.00%.

INACTIVE INGREDIENT

Other Ingredients: Water/Aqua/Eau, Glycerin, Dimethicone, Cetearyl Alcohol, C12-15 Alkyl Benzoate, Propylene Glycol, PEG-40 Hydrogenated Castor Oil, Potassium Cetyl Phosphate, Glyceryl Polyacrylate, Glyceryl Stearate, Butyrospermum Parkii (Shea Butter), Ergothioneine, Hydroxydecyl Ubiquinoyl Dipalmitoyl Glycerate, Sodium Hyaluronate, Hydrogenated Palm Glycerides, Sodium PCA, Trehalose, Urea, Polyquaternium-51, Carbomer, Sodium Hydroxide, Mica, Cylcohexasiloxane, Cyclopentasiloxane, Parfum/Fragrance, Alpha-Isomethyl Ionone, Linaloo, Benzoic Acid, Methylparaben, Phenoxyethanol, Chlorphenesin, Iron Oxisdes (CI 77492), Red 4 (CI 14700), Titanium Dioxide (CI 77891), Yellow 5 (CI 19140).

DOSAGE & ADMINISTRATION

Massage on to face and neck.

OTC - KEEP OUT OF REACH OF CHILDREN

Keep out of reach of children. If product is swallowed, get medical help or contact a Poison Control Center right away.

OTC - PURPOSE

Provides SPF 30 Sun Protection.

OTC - WHEN USING

Keep out of eyes.